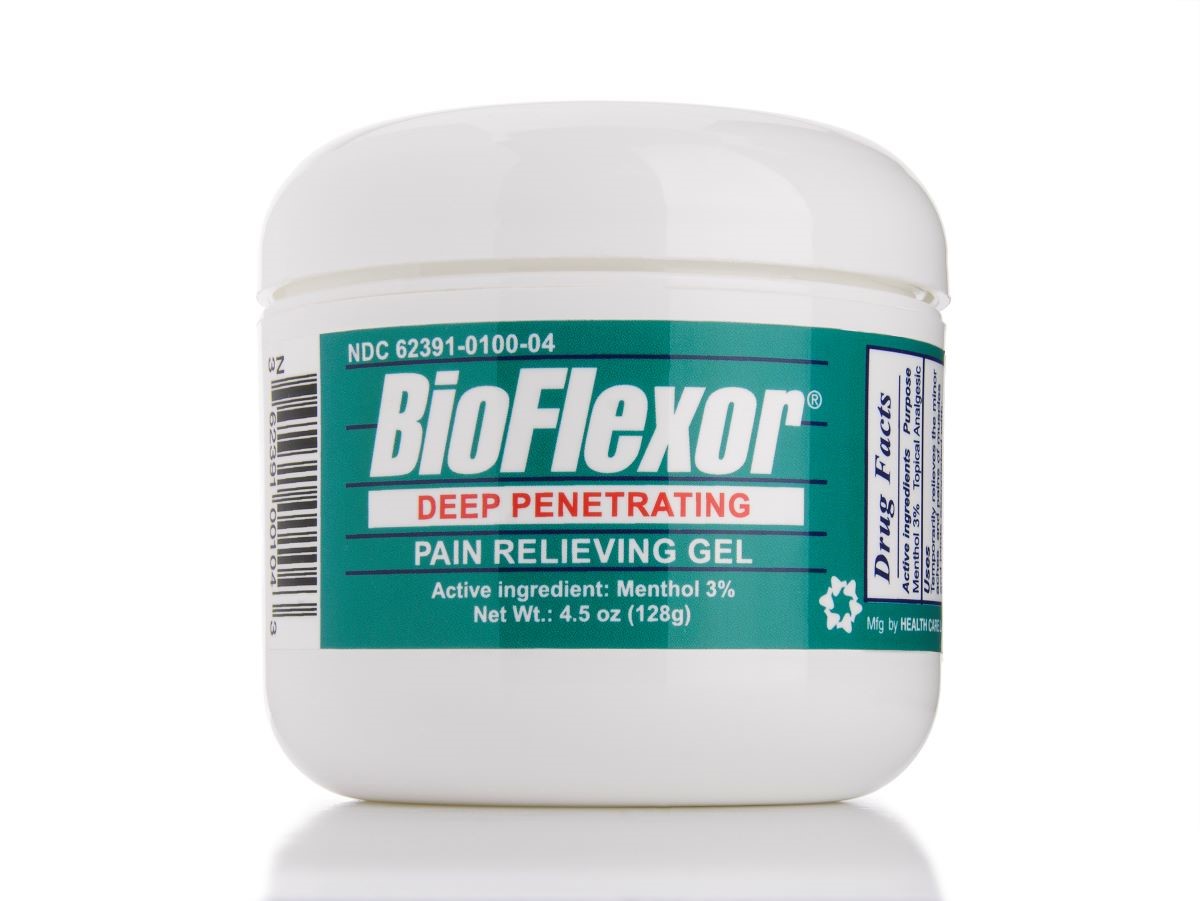 DRUG LABEL: BioFlexor
NDC: 62391-100 | Form: GEL
Manufacturer: Health Care Laboratories Inc.
Category: otc | Type: HUMAN OTC DRUG LABEL
Date: 20231212

ACTIVE INGREDIENTS: MENTHOL 3 g/100 g
INACTIVE INGREDIENTS: BUTYLPARABEN; CAMPHOR (SYNTHETIC); CARBOMER HOMOPOLYMER, UNSPECIFIED TYPE; EUCALYPTUS OIL; PHENOXYETHANOL; SODIUM HYDROXIDE; ILEX PARAGUARIENSIS LEAF; EDETATE DISODIUM; ETHYLPARABEN; METHYLPARABEN; PROPYLPARABEN; YUCCA SCHIDIGERA STEM; ALOE VERA LEAF; ISOBUTYLPARABEN; WATER; POTASSIUM SORBATE; POLYSORBATE 20

BioFlexor Deep Penetrating Gel

ACTIVE INGREDIENT

Active Ingredient: Purpose:

Menthol 3% ……………………………………………………………………Topical Analgesic

Purpose

Topical analgesic

INACTIVE INGREDIENTS

Inactive Ingredients: Aloe Vera Juice, Butyl Paraben, Camphor USP, Carbopol Polymer, Edetate Disodium, Ethyl Paraben, Eucalyptus Oil, Isobutyl Paraben, Methyl Paraben, Peacock Blue MX26, 2-Phenoxyethanol, Polysorbate 20, Potassium Sorbate, Propyl Paraben, Purified Water, Sodium Hydroxide, Yerba Mate, Yucca

WARNINGS SECTION

For external use only.

Keep out of reach of children. If swallowed, get medical help or contact the Poison Control Center right away.

Dosage and Administration

Directions

- Adults and children 12 years of age and older: apply to affected area not more than 3 to 4 times daily.
- Children under 12 years of age: consult a doctor

Uses

Temporarily relieves the minor aches and pains of muscles and joints associated with:

- simple backache
- arthritis
- strains
- bruises
- sprains

STORAGE AND HANDLING

Store at 15º-30ºC (59º-86ºF)

Do not use

• on wounds or damaged skin

• with a heating pad

• on a child under 12 years of age with arthritis-like conditions

Ask a doctor before use if you have redness over the affected area.

When using this product:

• avoid contact with the eyes or mucous membranes

• do not bandage tightly

Stop use and ask a doctor if:

• condition worsens or symptoms persist for more than 7 days

• symptoms clear up and occur again within a few days

• excessive skin irritation occurs

PRINCIPAL DISPLAY PANEL

Bioflexor